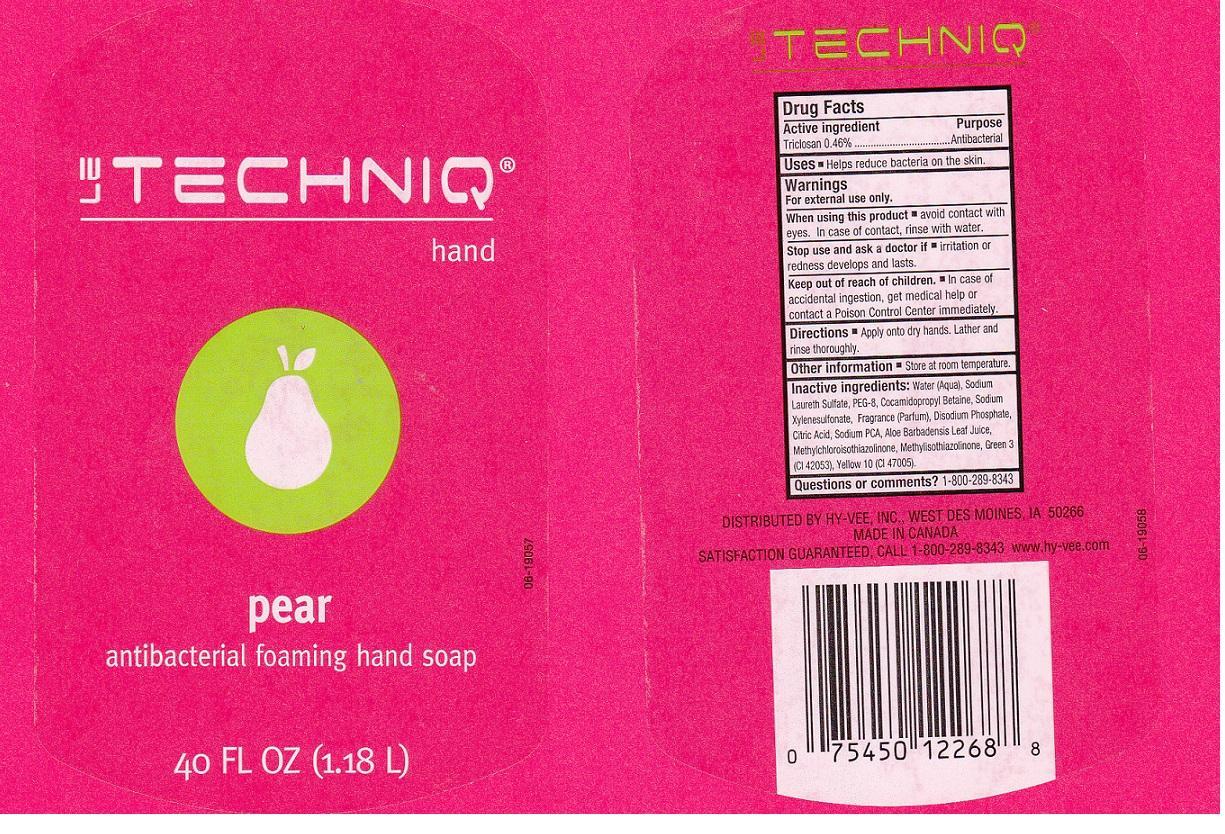 DRUG LABEL: LE TECHNIQ
NDC: 42507-113 | Form: LIQUID
Manufacturer: HYVEE INC
Category: otc | Type: HUMAN OTC DRUG LABEL
Date: 20130923

ACTIVE INGREDIENTS: TRICLOSAN 4.6 mg/1 mL
INACTIVE INGREDIENTS: WATER; SODIUM LAURETH SULFATE; POLYETHYLENE GLYCOL 400; COCAMIDOPROPYL BETAINE; SODIUM XYLENESULFONATE; SODIUM PHOSPHATE, DIBASIC ANHYDROUS; CITRIC ACID MONOHYDRATE; SODIUM PYRROLIDONE CARBOXYLATE; ALOE VERA LEAF; METHYLCHLOROISOTHIAZOLINONE; METHYLISOTHIAZOLINONE; FD&C GREEN NO. 3; D&C YELLOW NO. 10

DRUG FACTS

ACTIVE INGREDIENT

TRICLOSAN 0.46%

PURPOSE

ANTIBACTERIAL

USES

HELPS REDUCE BACTERIA ON THE SKIN.

WARNINGS

FOR EXTERNAL USE ONLY.

WHEN USING THIS PRODUCT

AVOID CONTACT WITH EYES. IN CASE OF CONTACT, RINSE WITH WATER.

STOP USE AND ASK A DOCTOR IF

IRRITATION OR REDNESS DEVELOPS AND LASTS.

KEEP OUT OF REACH OF CHILDREN

IN CASE OF ACCIDENTAL INGESTION, GET MEDICAL HELP OR CONTACT A POISON CONTROL CENTER IMMEDIATELY.

DIRECTIONS

APPLY ONTO DRY HANDS. LATHER AND RINSE THOROUGHLY.

OTHER INFORMATION

STORE AT ROOM TEMPERATURE.

INACTIVE INGREDIENTS:

WATER (AQUA), SODIUM LAURETH SULFATE, PEG-8, COCAMIDOPROPYL BETAINE, SODIUM XYLENESULFONATE, FRAGRANCE (PARFUM), DISODIUM PHOSPHATE, CITRIC ACID, SODIUM PCA, ALOE BARBADENSIS LEAF JUICE, METHYLCHLOROISOTHIAZOLINONE, METHYLISOTHIAZOLINONE, GREEN 3 (CI 42053), YELLOW 10 (CI 47005).

QUESTIONS OR COMMENTS?

1-800-289-8343